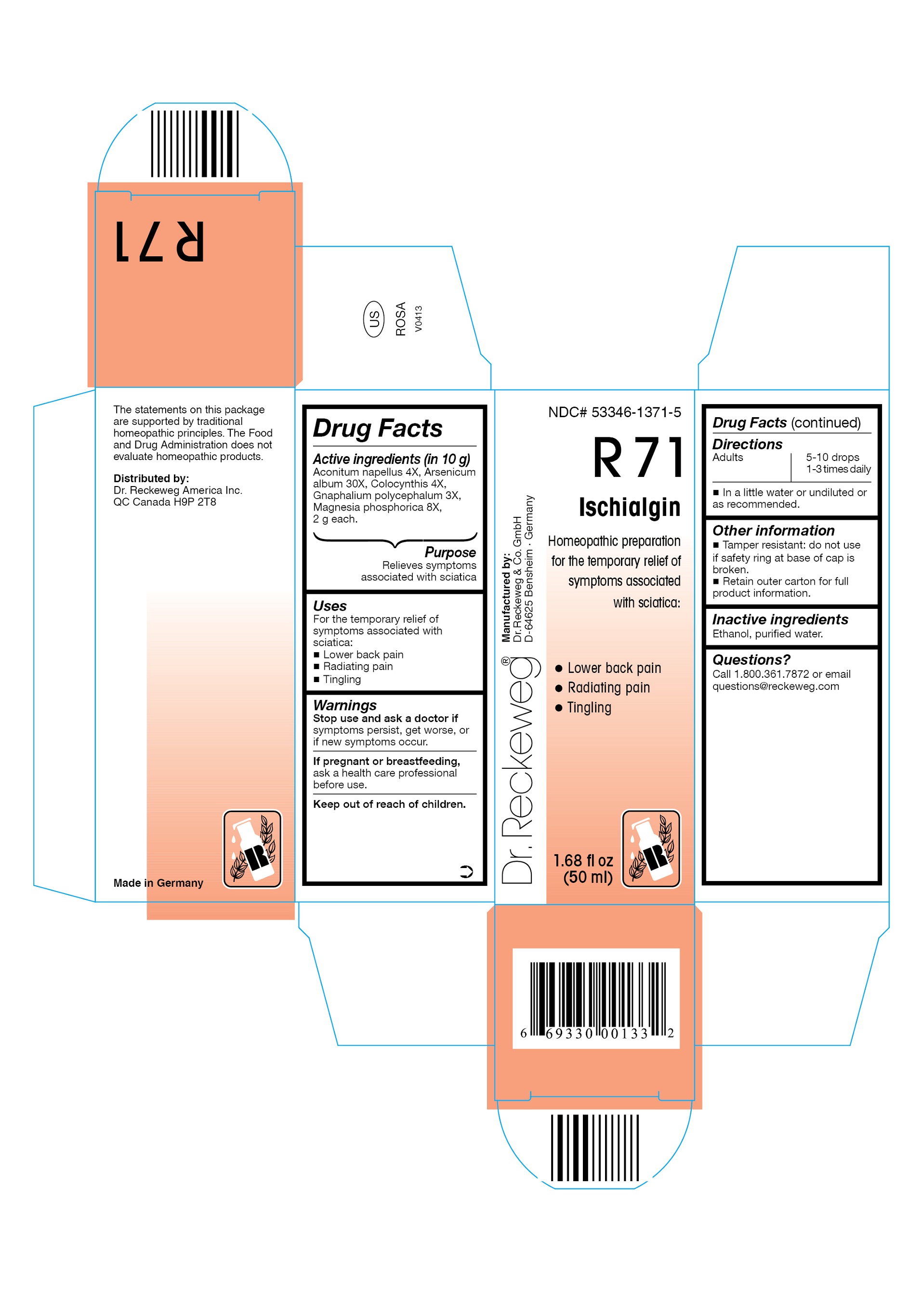 DRUG LABEL: DR. RECKEWEG R71 Ischialgin
NDC: 53346-1371 | Form: LIQUID
Manufacturer: PHARMAZEUTISCHE FABRIK DR. RECKEWEG & CO
Category: homeopathic | Type: HUMAN OTC DRUG LABEL
Date: 20130403

ACTIVE INGREDIENTS: ACONITUM NAPELLUS 4 [hp_X]/50 mL; ARSENIC TRIOXIDE 30 [hp_X]/50 mL; CITRULLUS COLOCYNTHIS FRUIT PULP 4 [hp_X]/50 mL; PSEUDOGNAPHALIUM OBTUSIFOLIUM 3 [hp_X]/50 mL; MAGNESIUM PHOSPHATE, DIBASIC TRIHYDRATE 8 [hp_X]/50 mL
INACTIVE INGREDIENTS: ALCOHOL; WATER

DR. RECKEWEG R71 Ischialgin

Active ingredients

Aconitum napellus 4X, Arsenicum album 30X, Colocynthis 4X, Gnaphalium polycephalum 3X, Magnesia phosphorica 8X, 2 g each in 10 g.

Purpose

Relieves of symptoms associated with sciatica

Uses

For the temporary relief of symptoms associated with sciatica:

- Lower back pain
- Radiating pain
- Tingling

Warnings

Stop use and ask a doctor if symptoms persist, get worse, or if new symptoms occur.

PREGNANCY OR BREAST FEEDING

If pregnant or breastfeeding, ask a health care professional before use.

Keep out of reach of children.

Directions
Adults 5-10 drops 1-3 times daily in a little water or undiluted or as recommended.

Other information

- Tamper resistant: do not use if safety ring at base of cap is broken.
- Retain outer carton for full product information.

Inactive ingredients

Ethanol, purified water.

Questions?
Call 1-800-361-7872 or email questions@reckeweg.com

PACKAGE LABEL

NDC# 53346-1371-5

Dr. Reckeweg R71 Ischialgin

Homeopathic preparation for the temporary relief of symptoms associated with sciatica:

- Lower back pain
- Radiating pain
- Tingling

Manufactured by:

Dr. Reckeweg Co. GmbH

D-64625 Bensheim

Germany

1.68 fl oz
(50 ml)